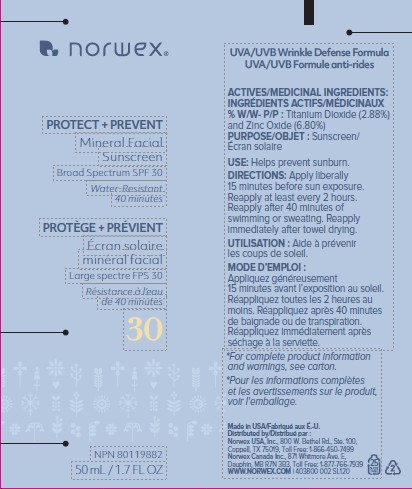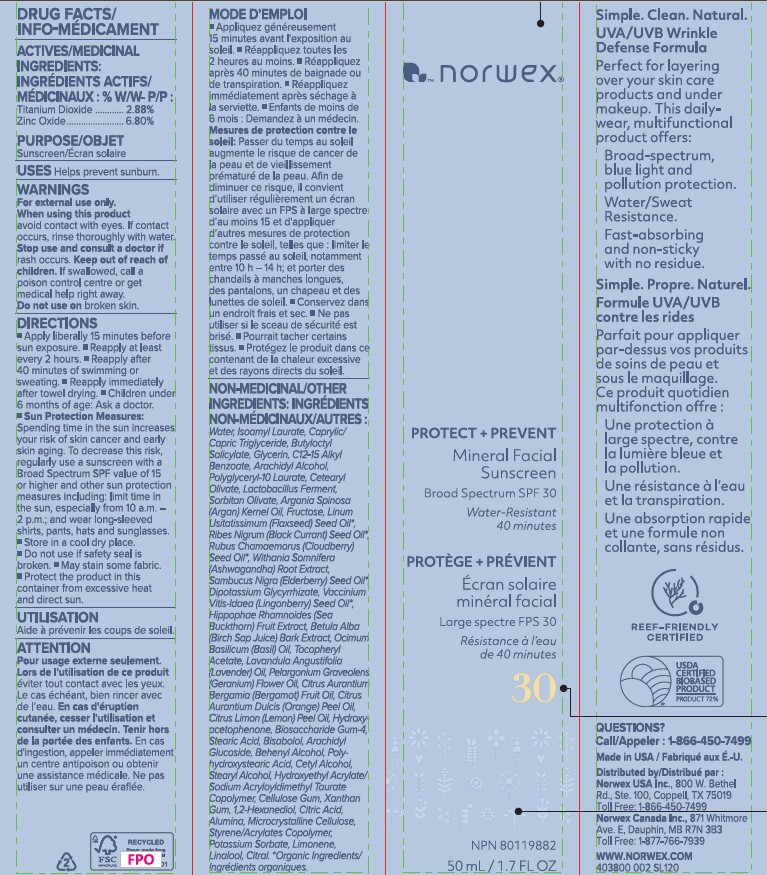 DRUG LABEL: Protect Prevent Daily Mineral Sunscreen Broad Spectrum SPF30
NDC: 80971-102 | Form: CREAM
Manufacturer: Norwex Usa, Inc.
Category: otc | Type: HUMAN OTC DRUG LABEL
Date: 20251120

ACTIVE INGREDIENTS: TITANIUM DIOXIDE 28.8 mg/1 mL; ZINC OXIDE 68 mg/1 mL
INACTIVE INGREDIENTS: ISOAMYL LAURATE; MEDIUM-CHAIN TRIGLYCERIDES; BUTYLOCTYL SALICYLATE; GLYCERIN; ALKYL (C12-15) BENZOATE; ARACHIDYL ALCOHOL; POLYGLYCERYL-10 LAURATE; CETEARYL OLIVATE; SORBITAN OLIVATE; ARGAN OIL; FRUCTOSE; FLAX SEED; RIBES NIGRUM SEED OIL; RUBUS CHAMAEMORUS SEED OIL; WITHANIA SOMNIFERA ROOT; WATER; SAMBUCUS NIGRA SEED OIL; GLYCYRRHIZINATE DIPOTASSIUM; LINGONBERRY SEED OIL; HIPPOPHAE RHAMNOIDES FRUIT; BETULA PUBESCENS BARK; BASIL OIL; .ALPHA.-TOCOPHEROL ACETATE; LAVENDER OIL; PELARGONIUM GRAVEOLENS FLOWER OIL; BERGAMOT OIL; ORANGE OIL, COLD PRESSED; LEMON OIL, COLD PRESSED; HYDROXYACETOPHENONE; BIOSACCHARIDE GUM-4; STEARIC ACID; LEVOMENOL; ARACHIDYL GLUCOSIDE; DOCOSANOL; CETYL ALCOHOL; STEARYL ALCOHOL; CARBOXYMETHYLCELLULOSE SODIUM, UNSPECIFIED; XANTHAN GUM; 1,2-HEXANEDIOL; CITRIC ACID MONOHYDRATE; ALUMINUM OXIDE; MICROCRYSTALLINE CELLULOSE; POTASSIUM SORBATE; LIMONENE, (+)-; LINALOOL, (+/-)-; CITRAL

Protect Prevent Daily Mineral Sunscreen Broad Spectrum SPF30

ACTIVES/MEDICINAL INGREDIENTS:% W/W- P/P:

Titanium Dioxide ............ 2.88%
Zinc Oxide........................ 6.80%

PURPOSE

Sunscreen

USES

Helps prevent sunburn.

WARNINGS

For external use only.

When using this product

avoid contact with eyes. If contact occurs, rinse thoroughly with water.

Stop use and consult a doctor if

rash occurs.

Keep out of reach of children.

If swallowed, call a poison control centre or get medical help right away.

Do not use

on broken skin.

DIRECTIONS

- Apply liberally 15 minutes before sun exposure.
- Reapply at least every 2 hours.
- Reapply after 40 minutes of swimming or sweating.
- Reapply immediately after towel drying.
- Children under 6 months of age: Ask a doctor.
- Sun Protection Measures: Spending time in the sun increases your risk of skin cancer and early skin aging. To decrease this risk, regularly use a sunscreen with a Broad Spectrum SPF value of 15 or higher and other sun protection measures including: limit time in the sun, especially from 10 a.m. – 2 p.m.; and wear long-sleeved shirts, pants, hats and sunglasses.
- Store in a cool dry place.
- Do not use if safety seal is broken.
- May stain some fabric.
- Protect the product in this container from excessive heat and direct sun.

NON-MEDICINAL/OTHER INGREDIENTS:

Water, Isoamyl Laurate, Caprylic/ Capric Triglyceride, Butyloctyl Salicylate, Glycerin, C12-15 Alkyl Benzoate, Arachidyl Alcohol, Polyglyceryl-10 Laurate, Cetearyl Olivate, Lactobacillus Ferment, Sorbitan Olivate, Argania Spinosa (Argan) Kernel Oil, Fructose, Linum Usitatissimum (Flaxseed) Seed Oil*, Ribes Nigrum (Black Currant) Seed Oil*, Rubus Chamaemorus (Cloudberry) Seed Oil*, Withania Somnifera (Ashwagandha) Root Extract, Sambucus Nigra (Elderberry) Seed Oil*, Dipotassium Glycyrrhizate, Vaccinium Vitis-Idaea (Lingonberry) Seed Oil*, Hippophae Rhamnoides (Sea Buckthorn) Fruit Extract, Betula Alba (Birch Sap Juice) Bark Extract, Ocimum Basilicum (Basil) Oil, Tocopheryl Acetate, Lavandula Angustifolia (Lavender) Oil, Pelargonium Graveolens (Geranium) Flower Oil, Citrus Aurantium Bergamia (Bergamot) Fruit Oil, Citrus Aurantium Dulcis (Orange) Peel Oil, Citrus Limon (Lemon) Peel Oil, Hydroxyacetophenone, Biosaccharide Gum-4, Stearic Acid, Bisabolol, Arachidyl Glucoside, Behenyl Alcohol, Polyhydroxystearic Acid, Cetyl Alcohol, Stearyl Alcohol, Hydroxyethyl Acrylate/ Sodium Acryloyldimethyl Taurate Copolymer, Cellulose Gum, Xanthan Gum, 1,2-Hexanediol, Citric Acid, Alumina, Microcrystalline Cellulose, Styrene/Acrylates Copolymer, Potassium Sorbate, Limonene, Linalool, Citral. *Organic Ingredients/ Ingrédients organiques.